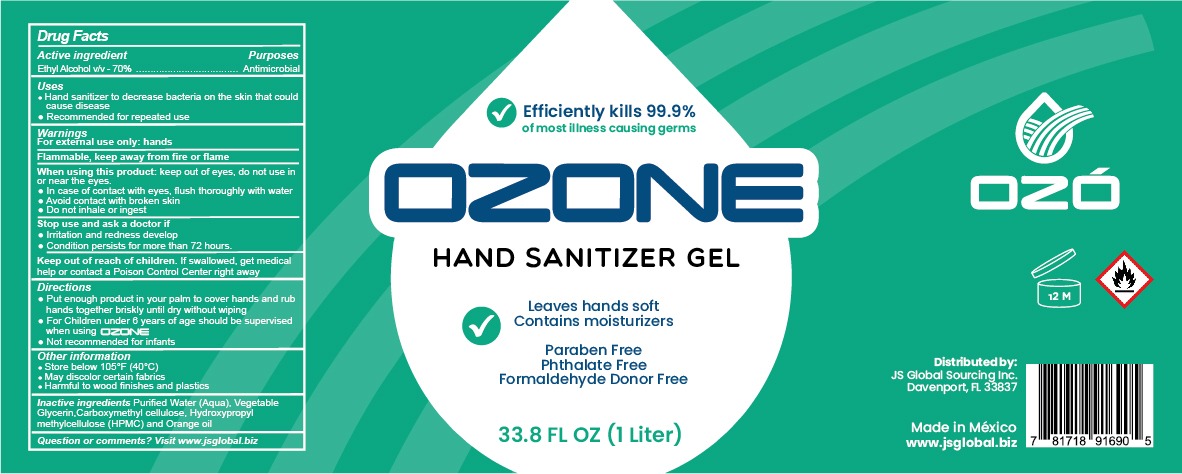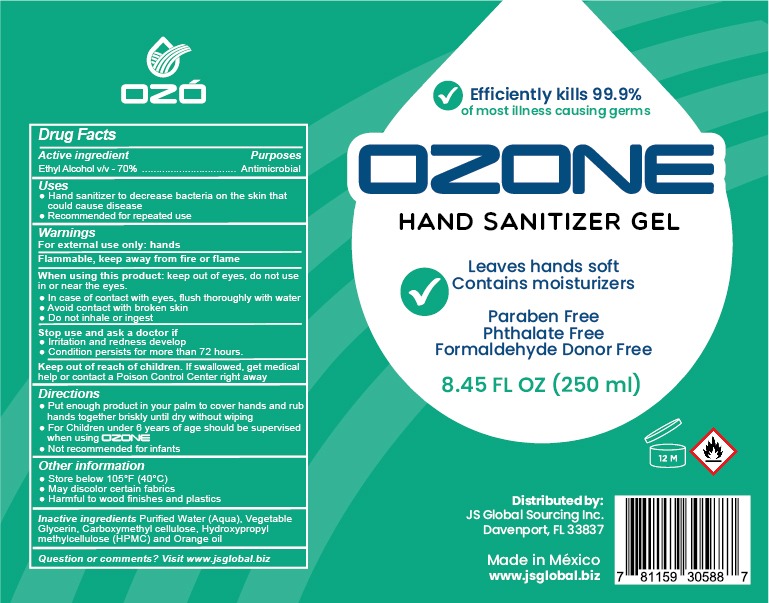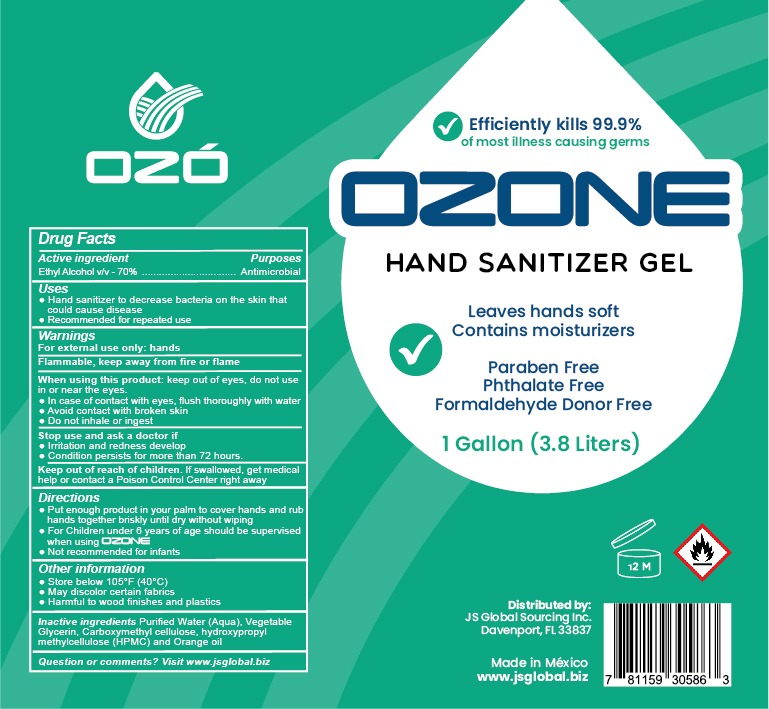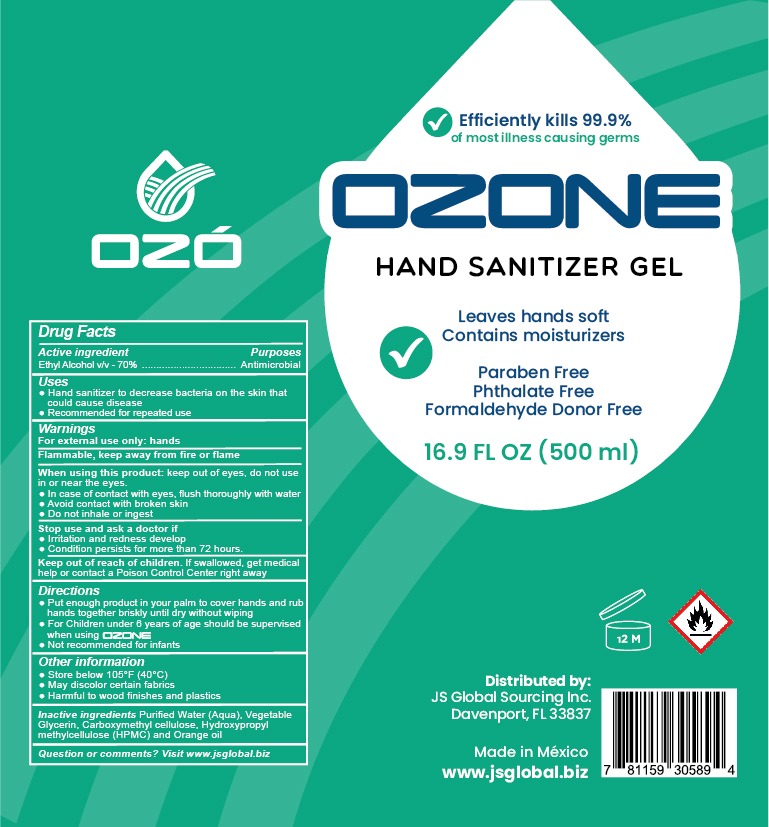 DRUG LABEL: HAND SANITIZER
NDC: 77210-0012 | Form: GEL
Manufacturer: EXPORTADORA IN & OUT S DE RL DE CV
Category: otc | Type: HUMAN OTC DRUG LABEL
Date: 20200629

ACTIVE INGREDIENTS: ALCOHOL 70 mL/100 mL
INACTIVE INGREDIENTS: GLYCERIN; ORANGE OIL; WATER; CARBOXYMETHYLCELLULOSE; HYPROMELLOSE 2208 (60000 MPA.S)

Active ingredient

ethyl alcohol v/v - 70%

Purposes

Antimicrobial

Uses

hand sanitizer to decrease bacteria on the skin that could cause disease

recommended for repetead use

warnings

for external use only: hands

flammable, keep away from fire and flame

When using this product

keep out of eyes, do not use in or near the eyes

in case of contact with eyes, flush thorougly with water

avoid contact with broken skin

do not inhale or ingest

When using this product

keep out of eyes, do not use in or near the eyes

in case of contact with eyes, flush thorougly with water

avoid contact with broken skin

stop use and ask a doctor if

irritation and redness develo

condition persists for more than 72 hours

Keep out of reach of children

if swallowed, get medical help or contact a posion control center right away

Directions

put enough product in your palm to cover hands and rub hands together briskly until dry without wiping

for children under 6 years of age should be supervised when using ozone

not recommended for infants

Other information

store below 105 F (40C)

may discolor certain fabrics

harmful to wood finishes and plastics

Inactive ingredients

Purified water (aqua), Vegetable Glycerin, Carboxymethyl cellulose, Hydroxypropyl methylcellulose hpmc, orange oil

Question or comments

visit www.jsglobal.biz

Principal Display

Efficiently kills 99.9%

of most illness causing germs

leaves hands soft

contain moisturizers

paraben free

phtalate free

formaldehyde donor free